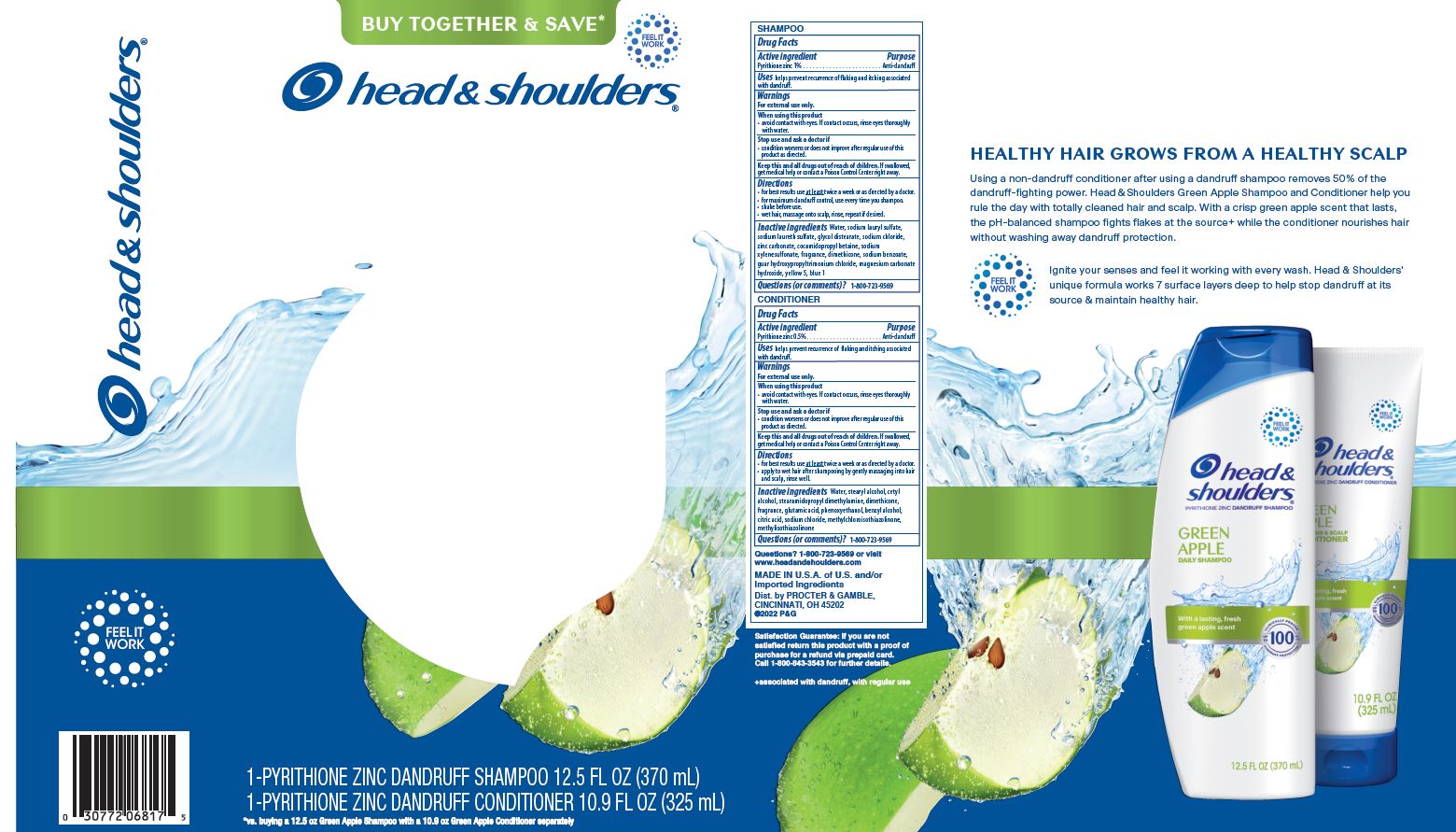 DRUG LABEL: Head and Shoulders Dual Pack Green Apple
NDC: 69423-209 | Form: KIT | Route: TOPICAL
Manufacturer: The Procter & Gamble Manufacturing Company
Category: otc | Type: HUMAN OTC DRUG LABEL
Date: 20241127

ACTIVE INGREDIENTS: PYRITHIONE ZINC 1 g/100 mL; PYRITHIONE ZINC 0.5 g/100 mL
INACTIVE INGREDIENTS: COCO MONOETHANOLAMIDE; GUAR HYDROXYPROPYLTRIMONIUM CHLORIDE (1.7 SUBSTITUENTS PER SACCHARIDE); WATER; SODIUM LAURETH-3 SULFATE; ZINC CARBONATE; GLYCOL DISTEARATE; SODIUM XYLENESULFONATE; DIMETHICONE; CETYL ALCOHOL; SODIUM CHLORIDE; SODIUM BENZOATE; MAGNESIUM CARBONATE HYDROXIDE; METHYLCHLOROISOTHIAZOLINONE; METHYLISOTHIAZOLINONE; STEARYL ALCOHOL; SODIUM LAURYL SULFATE; COCAMIDOPROPYL BETAINE; WATER; STEARYL ALCOHOL; CETYL ALCOHOL; STEARAMIDOPROPYL DIMETHYLAMINE; DIMETHICONE; GLUTAMIC ACID; PHENOXYETHANOL; BENZYL ALCOHOL; CITRIC ACID MONOHYDRATE; SODIUM CHLORIDE; METHYLCHLOROISOTHIAZOLINONE; METHYLISOTHIAZOLINONE

Head and Shoulders® Dual Kit
Green Apple

SHAMPOO

DRUG FACTS

Active ingredient

Pyrithione zinc 1%

Purpose

Anti-dandruff

Uses

helps prevent recurrence of flaking and itching associated with dandruff.

Warnings

For external use only.

When using this product

- avoid contact with eyes. If contact occurs, rinse eyes thoroughly with water.

Stop use and ask a doctor if

- condition worsens or does not improve after regular use of this product as directed.

KEEP OUT OF REACH OF CHILDREN

Keep this and all drugs out of reach of children.

If swallowed, get medical help or contact a Poison Control Center right away.

Directions

- for best results use at least twice a week or as directed by a doctor.
- for maximum dandruff control, use every time you shampoo.
- shake before use.
- wet hair, massage onto scalp, rinse, repeat if desired.

Inactive ingredients

Water, sodium lauryl sulfate, sodium laureth sulfate, glycol distearate, sodium chloride, zinc carbonate, cocamidopropyl betaine, sodium xylenesulfonate, fragrance, dimethicone, sodium benzoate, guar hydroxypropyltrimonium chloride, magnesium carbonate hydroxide, yellow 5, blue 1

Questions (or comments)?

1-800-723-9569

CONDITIONER

DRUG FACTS

Active ingredient

Pyrithione zinc 0.5%

Purpose

Anti-dandruff

Uses

helps prevent recurrence of flaking and itching associated with dandruff.

Warnings

For external use only.

When using this product

- avoid contact with eyes. If contact occurs, rinse eyes thoroughly with water.

Stop use and ask a doctor if

- condition worsens or does not improve after regular use of this product as directed.

KEEP OUT OF REACH OF CHILDREN

Keep this and all drugs out of reach of children.

If swallowed, get medical help or contact a Poison Control Center right away.

Directions

- for best results use at least twice a week or as directed by a doctor.
- apply to wet hair after shampooing by gently massaging into hair and scalp, rinse well.

Inactive ingredients

Water, stearyl alcohol, cetyl alcohol, stearamidopropyl dimethylamine, dimethicone, fragrance, glutamic acid, phenoxyethanol, benzyl alcohol, citric acid, sodium chloride, methylchloroisothiazolinone, methylisothiazolinone.

Questions (or comments)?

1-800-723-9569

Dist. by PROCTER & GAMBLE,
CINCINNATI, OH 45202

PRINCIPAL DISPLAY PANEL - Kit Package

head and shoulders

1 PYRITHIONE ZINC DANDRUFF SHAMPOO 12.5 FL OZ (370 mL)

1 PYRITHIONE ZINC DANDRUFF CONDITIONER 10.9 FL OZ (325 mL)